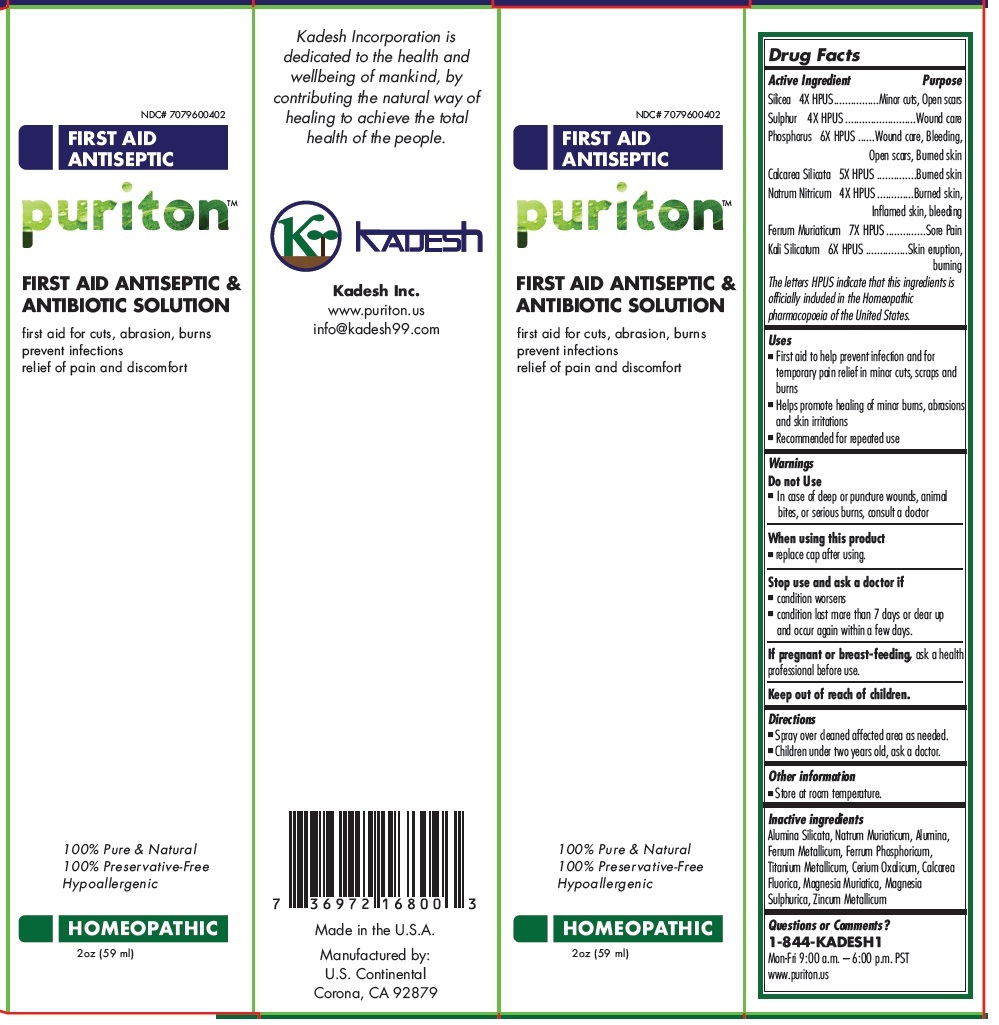 DRUG LABEL: Puriton FIRST AID ANTISEPTIC AND ANTIBIOTIC Solution
NDC: 70796-004 | Form: SPRAY
Manufacturer: Kadesh, Inc.
Category: homeopathic | Type: HUMAN OTC DRUG LABEL
Date: 20161209

ACTIVE INGREDIENTS: SILICON DIOXIDE 4 [hp_X]/59 mL; SULFUR 4 [hp_X]/59 mL; PHOSPHORUS 6 [hp_X]/59 mL; CALCIUM SILICATE 5 [hp_X]/59 mL; SODIUM NITRATE 4 [hp_X]/59 mL; FERRIC CHLORIDE HEXAHYDRATE 7 [hp_X]/59 mL; POTASSIUM SILICATE 6 [hp_X]/59 mL
INACTIVE INGREDIENTS: KAOLIN; SODIUM CHLORIDE; ALUMINUM OXIDE; IRON; FERROSOFERRIC PHOSPHATE; TITANIUM; CEROUS OXALATE NONAHYDRATE; CALCIUM FLUORIDE; MAGNESIUM CHLORIDE; MAGNESIUM SULFATE HEPTAHYDRATE; ZINC

Puriton FIRST AID ANTISEPTIC & ANTIBIOTIC SOLUTION

Active Ingredient

Silicea 4X HPUS

Sulphur 4X HPUS

Phosphorus 6X HPUS

Calcarea Silicata 5X HPUS

Natrum Nitricum 4X HPUS

Ferrum Muriaticum 7X HPUS

Kali Silicatum 6X HPUS

The letters HPUS indicate that this ingredients is officially included in the Homeopathic pharmacopoeia of the United States.

Purpose

Minor cuts, Open scars
Wound care
Wound care, Bleeding, Open scars, Burned skin
Burned skin
Burned skin, Inflamed skin, bleeding
Sore Pain
Skin eruption, burning

Uses

- First aid to help prevent infection and for temporary pain relief in minor cuts, scraps and burns
- Helps promote healing of minor burns, abrasions and skin irritations
- Recommended for repeated use

Warnings

Do not Use

• In case of deep or puncture wounds, animal bites, or serious burns, consult a doctor

When using this product

• replace cap after using.

Stop use and ask a doctor if

• condition worsens

• condition last more than 7 days or clear up and occur again within a few days.

If pregnant or breast-feeding, ask a health professional before use.

Keep out of reach of children.

Directions

- Spray over cleaned affected area as needed.
- Children under two years old, ask a doctor.

Other information

- Store at room temperature.

Inactive ingredients

Alumina Silicata, Natrum Muriaticum, Alumina, Ferrum Metallicum, Ferrum Phosphoricum, Titanium Metallicum, Cerium Oxalicum, Calcarea Fluorica, Magnesia Muriatica, Magnesia Sulphurica, Zincum Metallicum

Questions or Comments?

1-844-KADESH1
Mon-Fri 9:00 a.m. – 6:00 p.m. PST
www.puriton.us

first aid for cuts, abrasion, burns
prevent infections
relief of pain and discomfort
100% Pure & Natural
100% Preservative-Free
Hypoallergenic
Made in the U.S.A.
Manufactured by:
U.S. Continental
Corona, CA 92879